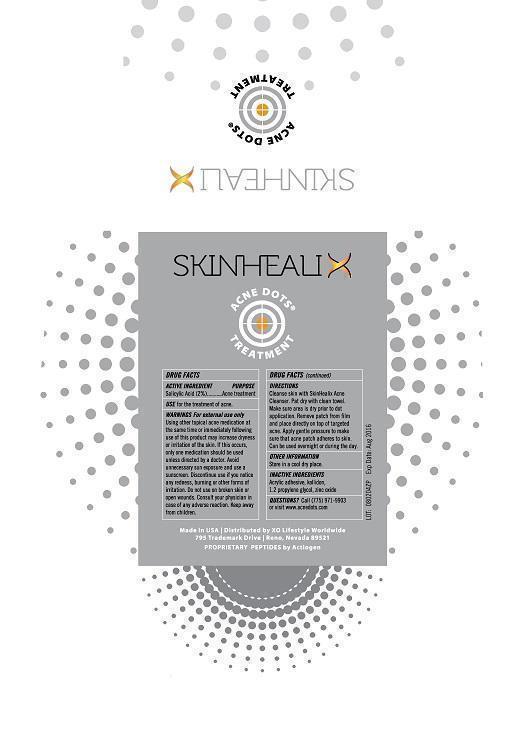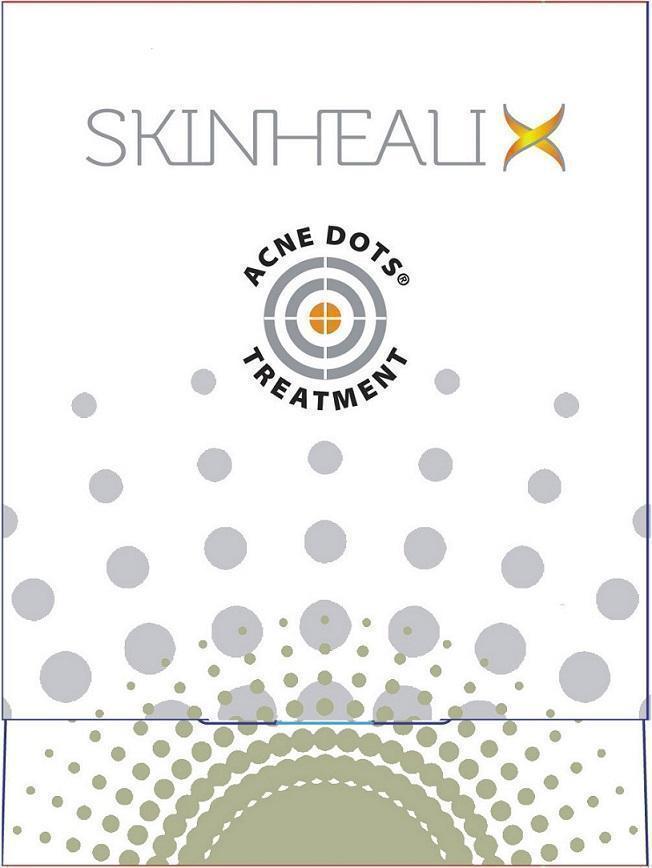 DRUG LABEL: Actiogen Acne Dots Treatment
NDC: 69186-001 | Form: PATCH
Manufacturer: Actiogen Corp
Category: otc | Type: HUMAN OTC DRUG LABEL
Date: 20150714

ACTIVE INGREDIENTS: SALICYLIC ACID 2 mg/100 mg
INACTIVE INGREDIENTS: ACRYLIC ACID 96 mg/100 mg; PROPYLENE GLYCOL 1 mg/100 mg; ZINC OXIDE 1 mg/100 mg

Actiogen Acne Dots

Active Ingredients

Salicylic Acid 2%

Purpose

Acne Treatment

Use

For the treatment of acne

Warnings

For external use only

When Using This Product

Using other topical acne medication at the same time or immediately following use of this product may increase dryness or irritation of the skin. If this occurs, only one medication should be used unless directed by a doctor

Stop Using This Product

Discontinue use if you notice an redness, burning, or other forms of irritation

Do not use on broken skin or open wounds

Consult a physician

Consult your physician in case of adverse reaction

Keep Out of Reach of Children

Keep away from children

Other Information

Store in a cool dry place.

Inactive Ingredients

Acrylic adhesive, kollidon, 1,2 Propylene Glycol, Zinc Oxide

PACKAGE LABEL

Front of Box